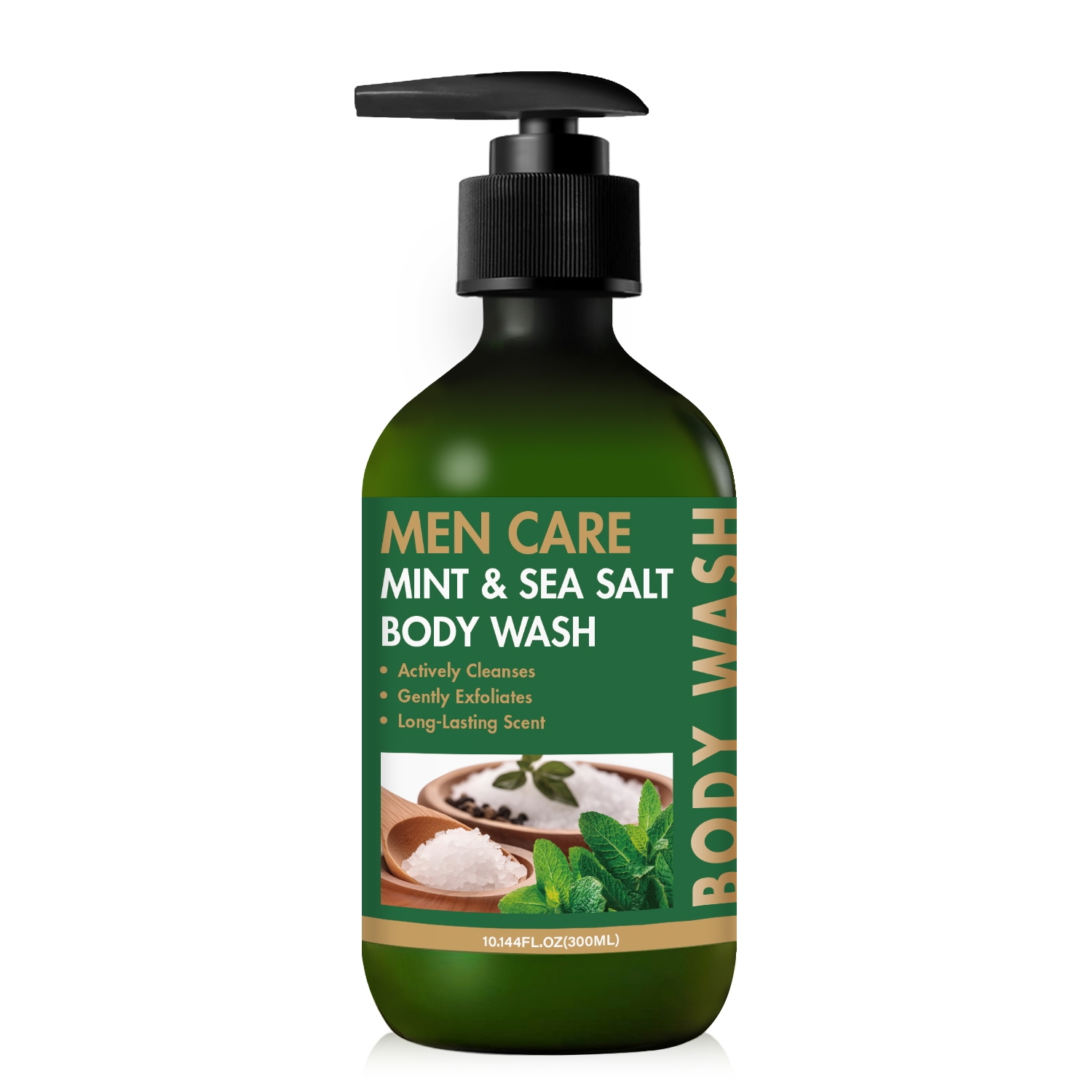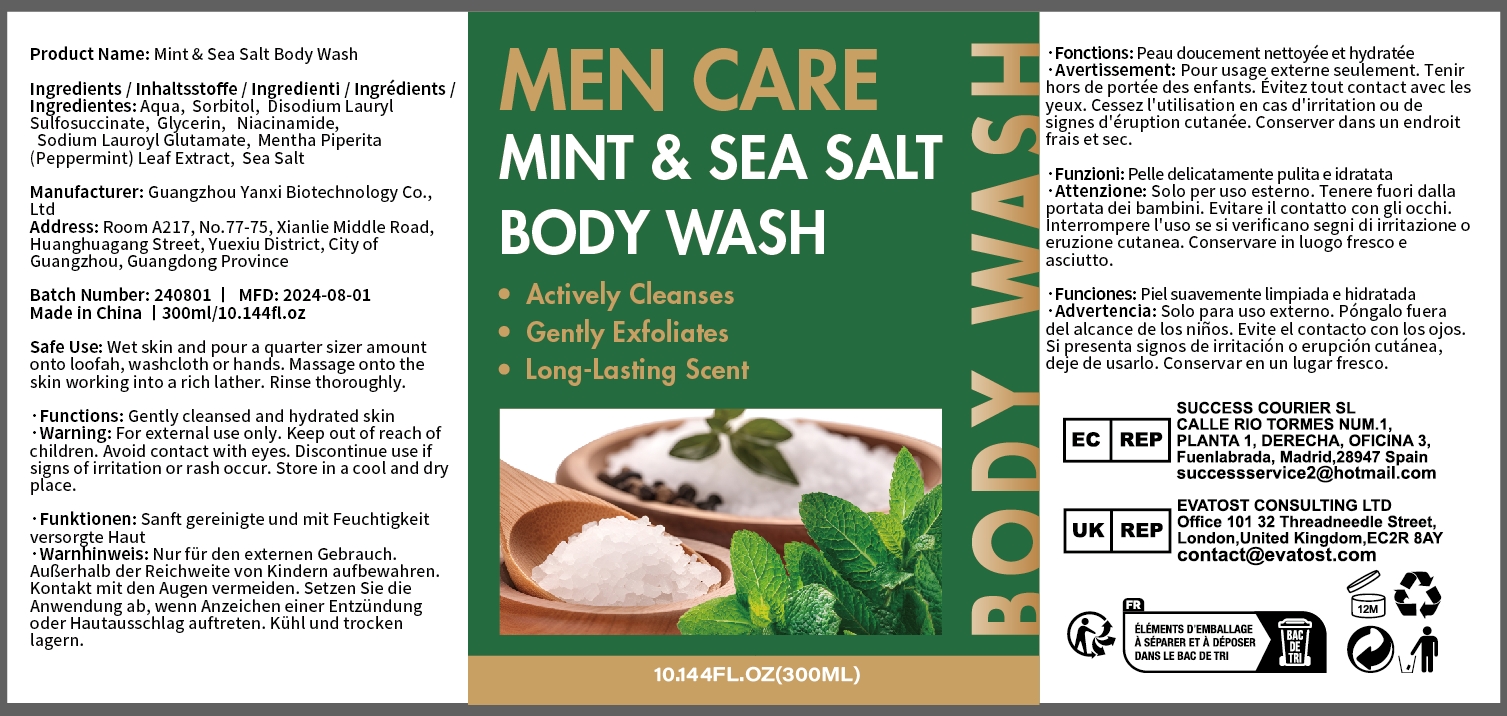 DRUG LABEL: Mint Sea Salt Body Wash
NDC: 84025-286 | Form: CREAM
Manufacturer: Guangzhou Yanxi Biotechnology Co., Ltd
Category: otc | Type: HUMAN OTC DRUG LABEL
Date: 20241219

ACTIVE INGREDIENTS: NIACINAMIDE 8 mg/300 mL; GLYCERIN 9 mg/300 mL
INACTIVE INGREDIENTS: WATER

DOSAGE AND ADMINISTRATION

Clean The Private Parts, Squeeze Out The Right Amount Of Cream And Smear The Required Parts

WARNINGS

Keep out of children

INACTIVE INGREDIENT

Aqua

INDICATIONS AND USAGE

For daily skin care

Keep out of children

PURPOSE

Gentlycleansed and hydrated skin